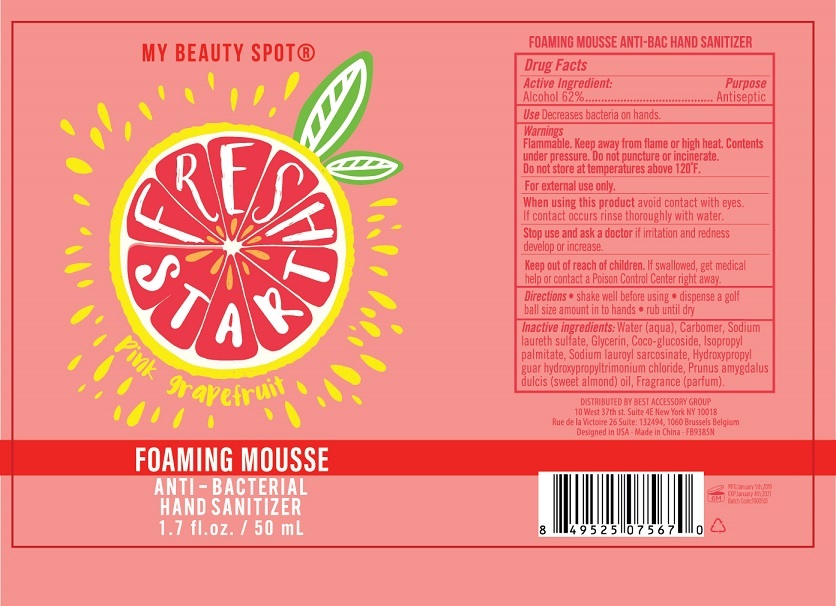 DRUG LABEL: Foaming Mousse Anti-Bacterial Hand Sanitizer
NDC: 56136-023 | Form: AEROSOL, FOAM
Manufacturer: Ganzhou Olivee Cosmetic Co., Ltd.
Category: otc | Type: HUMAN OTC DRUG LABEL
Date: 20181201

ACTIVE INGREDIENTS: alcohol 62 mL/100 mL
INACTIVE INGREDIENTS: WATER; PROPYLENE GLYCOL; SODIUM LAURETH SULFATE; CARBOMER 934; GLYCERIN; COCO GLUCOSIDE; ISOPROPYL PALMITATE; SODIUM LAUROYL SARCOSINATE; HYDROXYPROPYL GUAR (2500-4500 MPA.S AT 1%); HYDROXYPROPYL TRIMONIUM CHLORIDE

Drug facts

Active ingredient Purpose

Alcohol 62% ... Antiseptic

PURPOSE

Decrease bacteria on hands.

KEEP OUT OF REACH OF CHILDREN

If swallowed, get medical help or contact local poison control center right away.

INDICATIONS AND USAGE

Avoid contact with eyes， if contact occurs rinse thoroughly with water.

DOSAGE AND ADMINISTRATION

- shake well before using
- dispense a golf ball size amount in to hands
- rub until dry

WARNINGS

For external use only.
Flammable. Keep product away from flame or high heat. Contents under pressure. Do not puncture or incinerate.

Stop using and ask a doctor, if irritation and redness develop or increase.

INACTIVE INGREDIENT

Water (aqua), Carbomer, Sodium laureth sulfate, Glycerin, Coco-glucoside, Isopropyl palmitate, Sodium laureyl sarcosinate, Hydroxypropyl guar, Hydroxypropyl trimonium chloride, Prunus amygdalus dulcis (sweet almond) oil, Fragrance (parfum).